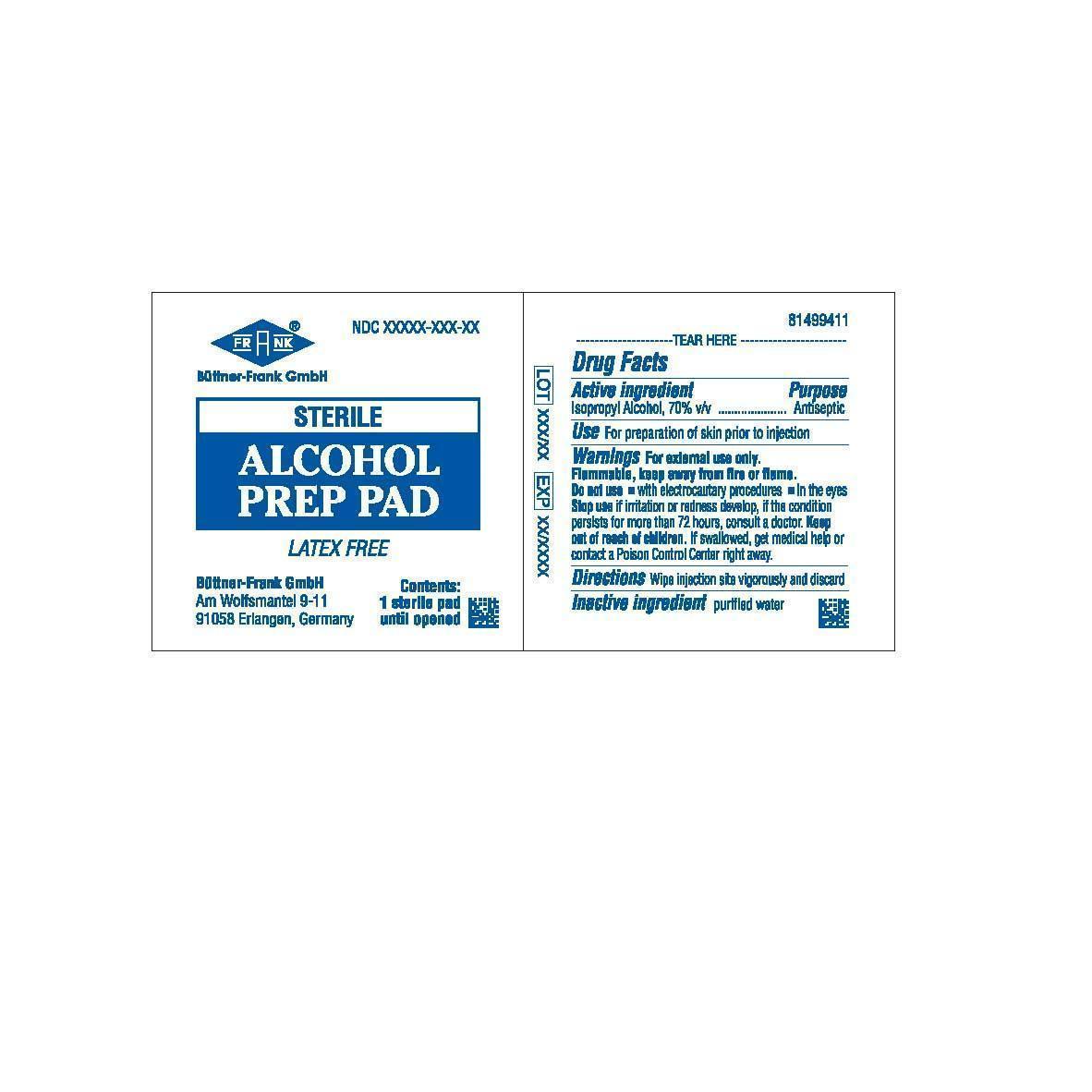 DRUG LABEL: Alcohol Prep Pad
                
NDC: 36769-002 | Form: SWAB
Manufacturer: Büttner-Frank GmbH Arzt- und Krankenhausbedarf - Krankenpflege und Einmalartikel
Category: otc | Type: HUMAN OTC DRUG LABEL
Date: 20130123

ACTIVE INGREDIENTS: ISOPROPYL ALCOHOL .70 mg/1 mg
INACTIVE INGREDIENTS: WATER

Active Ingredient

Isopropyl Alcohol 70% v/v

Inactive Ingredient

Purified Water

Purpose

Antiseptic

Use

For Preparation of skin prior to injection

Keep Out of Reach of Children

Directions

Wipe Injection site vigorously and discard

Warnings

For external use only. Flammable, keep away from fire or flame.

Do not use

- With electrocautary procedures

- In the eyes.

Stop use if irritation or redness develop. If the condition persists for more than 72 hours consult a doctor.
If swallowed, get medical help or contact a Poison Control Center right away.

Package Label

Sterile Alcohol Prep Pad Latex Free

Buttner-Frank GmbH Am Wolfsmantel 9-11 91058 Erlangen, Germany

Contents: 1 sterile pad until opened

LOT_____________ EXP _________________ NDC _____________________

Tear Here